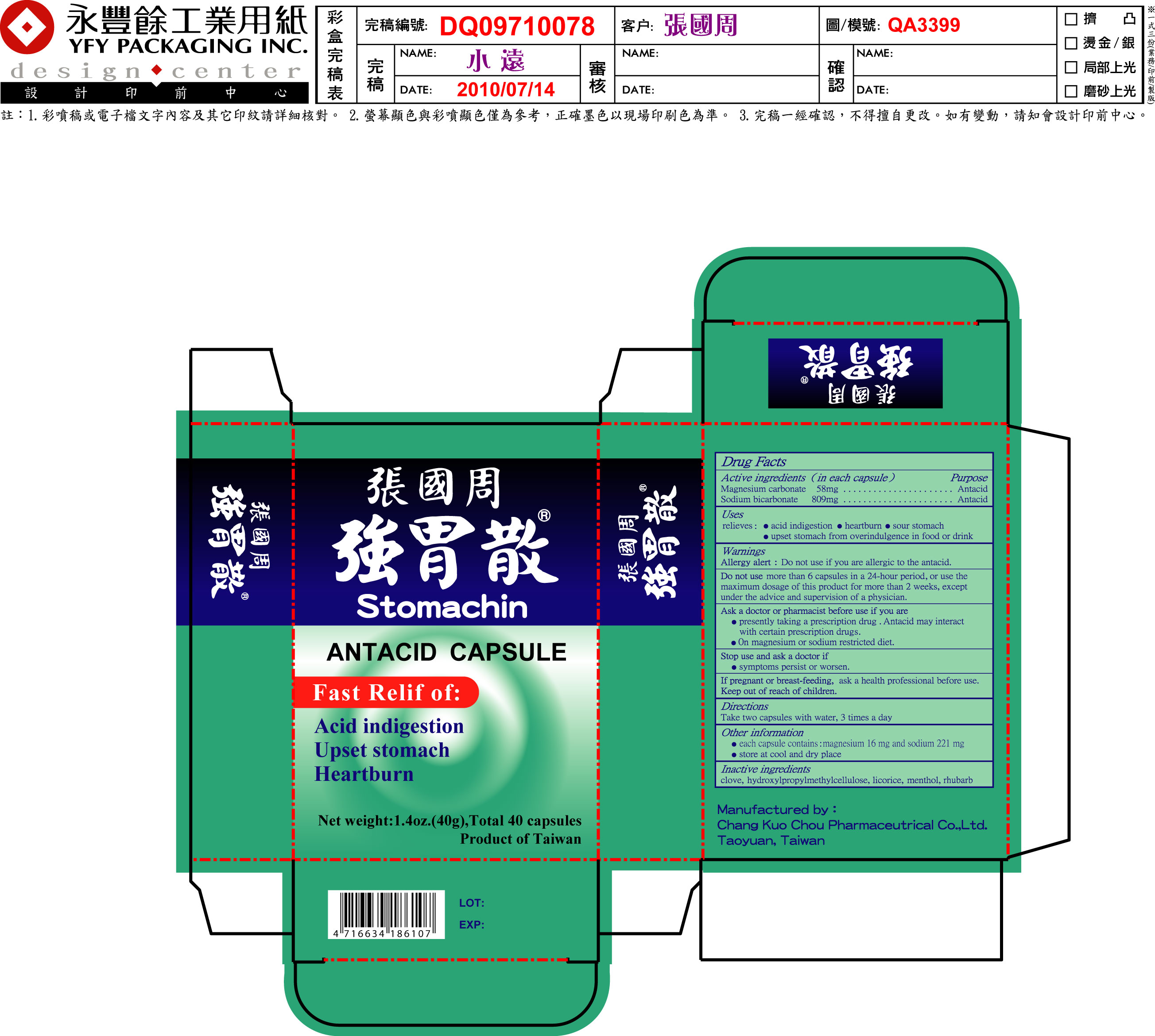 DRUG LABEL: Stomachin Antacid
NDC: 43337-9328 | Form: CAPSULE
Manufacturer: Chang Kuo Chou Pharmaceutical Co. Ltd.
Category: otc | Type: HUMAN OTC DRUG LABEL
Date: 20110817

ACTIVE INGREDIENTS: Magnesium carbonate 58 mg/1 g; Sodium bicarbonate 809 mg/1 g
INACTIVE INGREDIENTS: Clove 29 mg/1 g; Hydroxypropyl Cellulose; Licorice 86 mg/1 g; Menthol 4 mg/1 g; Rhubarb 14 mg/1 g

"Drug Facts"

Active ingredients (in each capsule) Purpose

Magnesium carbonate 58mg ................... Antacid

Sodium bicarbonate 809mg .................... Antacid

Uses

- acid indigestion
- heartburn
- sour stomach
- upset stomach from overindulgence in food or drink

Stop use and as a doctor if

- symptoms persit or worsen

Keep out of reach of children

PREGNANCY OR BREAST FEEDING

If pregnant of breast feeding, ask a health professional before use.

INDICATIONS AND USAGE

Antacid

Directions

TAke two capsules with water 3 times a day

Do not use

more than 6 capsules in a 24-hour period, or use the maximum dosage of this product for more than 2 weeks, expect under the advice and supervision of a physician.

Inactive ingredients

clove, hydroxypropyl cellulose, licorice, menthol, rhubarb

Ask a doctor or pharmacist before use if you are

- presently taking a prescription drug. Antacid may interact with certain prescription drugs
- on magnesium or sodium restrict diet.

PACKAGE LABEL

Enter section text here